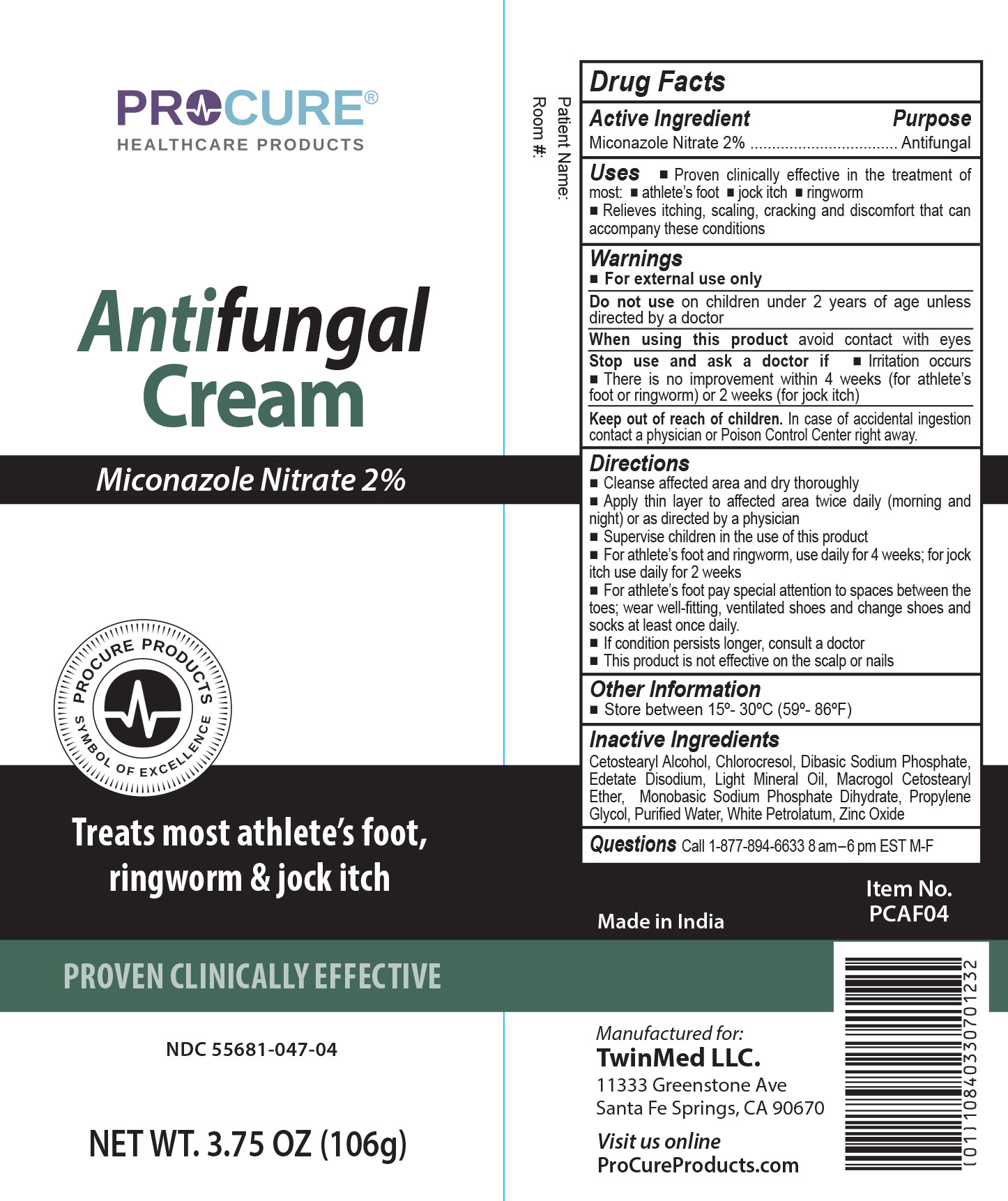 DRUG LABEL: ProCure Antifungal
NDC: 55681-047 | Form: CREAM
Manufacturer: Twin Med LLC
Category: otc | Type: HUMAN OTC DRUG LABEL
Date: 20260128

ACTIVE INGREDIENTS: MICONAZOLE NITRATE 2 g/100 g
INACTIVE INGREDIENTS: SODIUM PHOSPHATE, DIBASIC, UNSPECIFIED FORM; CETOSTEARYL ALCOHOL; POLYOXYL 20 CETOSTEARYL ETHER; SODIUM PHOSPHATE, MONOBASIC, DIHYDRATE; CHLOROCRESOL; EDETATE DISODIUM; LIGHT MINERAL OIL; PROPYLENE GLYCOL; WATER; WHITE PETROLATUM; ZINC OXIDE

Active Ingredient

Miconazole Nitrate 2%

Purpose

Antifungal

Uses

- Proven clinically effective in the treatment of most Athlete's foot, jock itch and ring worm
- Relieves itching, scaling, cracking and discomfort that can accompany these conditions

Warnings

For external use only

Do not use on children under 2 years of age unless directed by a doctor

When using this product avoid contact with eyes

Stop using and ask a doctor if

- irritation occurs
- there is no improvement within 4 weeks (for athlete’s foot or ringworm) or 2 weeks (for jock itch)

Keep out of reach of Children. In case of accidental ingestion, contact a physician or Poison Control Center right away.

Directions

- Cleanse affected area and dry thoroughly
- Apply thin layer to affected area twice daily (morning and night) or as directed by a physician
- Supervise children in the use of this product
- For athlete’s foot and ringworm, use daily for 4 weeks; for jock itch use daily for 2 weeks
- For athlete’s foot pay special attention to space between the toes; wear well-fitting, ventilated shoes and change shoes and socks at least once daily.
- This product is not effective on the scalp or nails

Inactive Ingredients

Inactive Ingredients: Cetostearyl Alcohol, Chlorocresol, Dibasic Sodium Phosphate, Edetate Disodium, Light Mineral Oil, Macrogol Cetostearyl Ether, Monobasic Sodium Phosphate Dihydrate, Propylene Glycol, Purified Water, White Petrolatum, Zinc Oxide